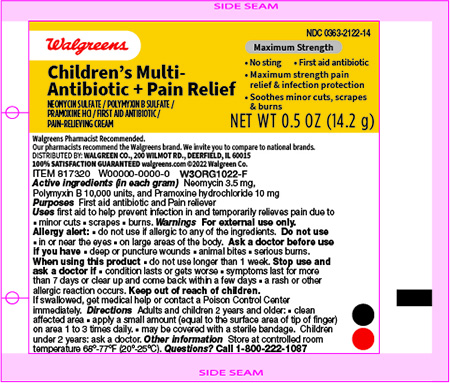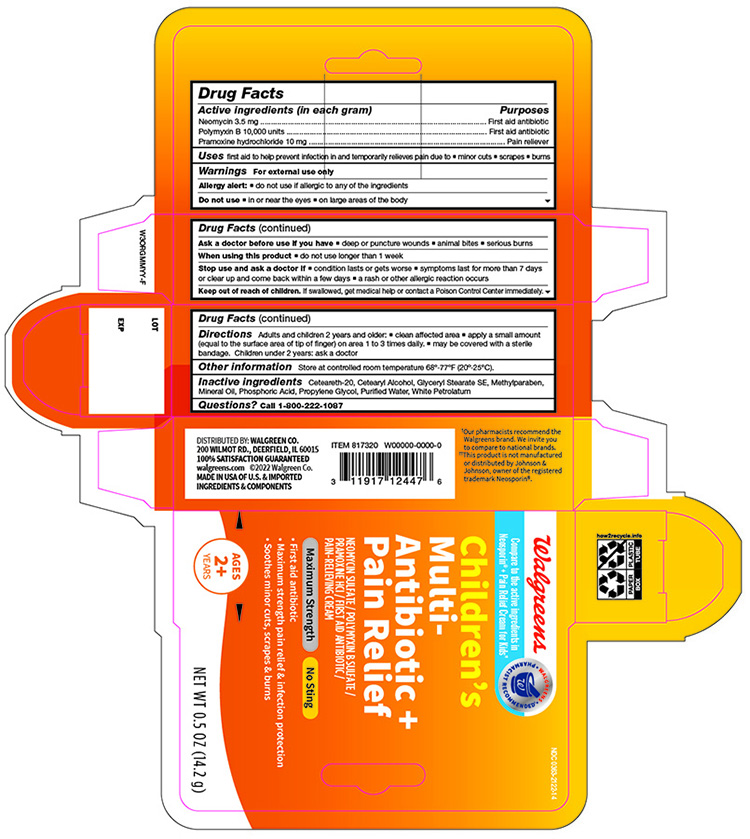 DRUG LABEL: Walgreens Kids Multi-Antibiotic with Pain Relief Cream
NDC: 0363-2122 | Form: CREAM
Manufacturer: Walgreens Company
Category: otc | Type: HUMAN OTC DRUG LABEL
Date: 20241120

ACTIVE INGREDIENTS: POLYMYXIN B SULFATE 10000 [USP'U]/1 g; NEOMYCIN SULFATE 3.5 mg/1 g; PRAMOXINE HYDROCHLORIDE 10 mg/1 g
INACTIVE INGREDIENTS: POLYOXYL 20 CETOSTEARYL ETHER; CETOSTEARYL ALCOHOL; GLYCERYL STEARATE SE; METHYLPARABEN; MINERAL OIL; PHOSPHORIC ACID; PROPYLENE GLYCOL; WATER; WHITE PETROLATUM

Active ingredients (in each gram) Purpose

Neomycin Sulfate (3.5mg) First Aid Antibiotic
Polymixin B Sulfate (10,000 units) First Aid Antibiotic
Pramoxine Hydrochloride (10 mg) External Analgesic

Purpose

First Aid Antibiotic

First Aid Antibiotic

External Analgesic

Uses

first aid to prevent infection and for the temporary relief of pain or discomfort in minor:

cuts
scapes
burns

Warnings

For external use only

Keep this and all drugs out of the reach of children

If swallowed, get medical help or contact Poison Control Center right away.

Directions

Adults and children 2 years of age and older:

- clean the affected area
- apply a small amount of this product (an amount equal to the surface area of the tip of a finger) on the area 1 to 3 times daily
- may be covered with a sterile bandage
- children under 2 years of age: ask a doctor

Other Information

store at 20° to 25°C (68° to 77°F)

Inactive ingredients

Ceteareth-20, Cetearyl Alcohol, Glyceryl Stearate SE, Methylparaben, Mineral Oil, Phosphoric Acid, Propylene Glycol, Purified Water, White Petrolatum

Questions?

Call 1-800-222-1087

Principal Display Panel -Tube

Walgreens Children Multi Antibiotic +Pain Relief Cream NDC 0363-2122-14

Neomycin Sulfate /Polymxin B Sulfate /Pramoxine HCL

First Aid Anitbiotic / Pain Relieving Cream

NET WT 0.5 OZ (14.2g)

Principal Dispaly Panel -Carton

Walgreens Children Multi Antibiotic +Pain Relief Cream NDC 0363-2122-14

Neomycin Sulfate /Polymxin B Sulfate /Pramoxine HCL

First Aid Anitbiotic / Pain Relieving Cream

NET WT 0.5 OZ (14.2g)